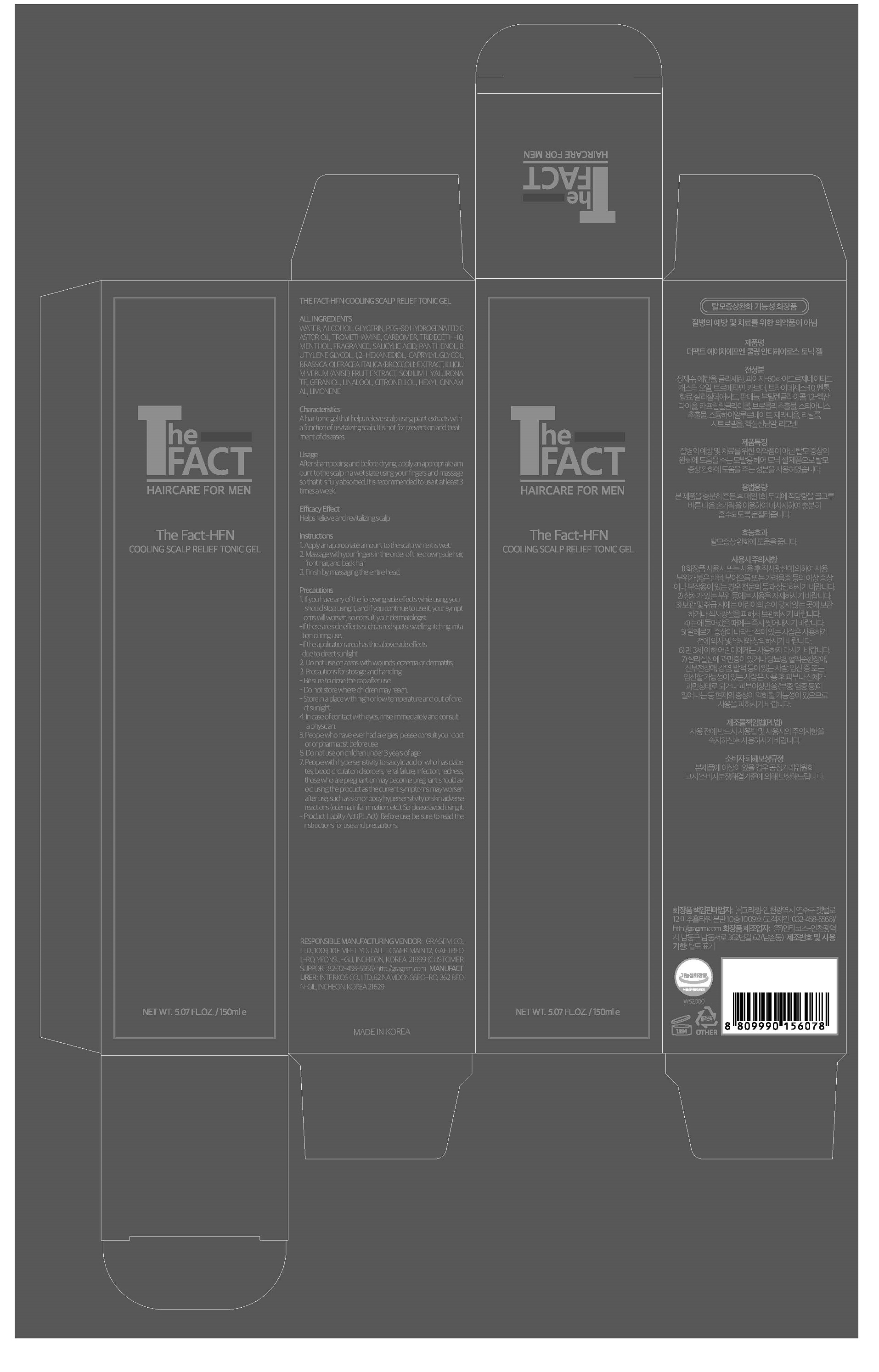 DRUG LABEL: The Fact-HFN Cooling Anti-hair Loss TonicGel
NDC: 77049-0011 | Form: GEL
Manufacturer: Interkos Co.,Ltd.
Category: otc | Type: HUMAN OTC DRUG LABEL
Date: 20220120

ACTIVE INGREDIENTS: PANTHENOL 0.3 g/100 mL; MENTHOL 0.04 g/100 mL; SALICYLIC ACID 0.25 g/100 mL
INACTIVE INGREDIENTS: WATER

Drug Facts

ACTIVE INGREDIENT

menthol

salicylic acid

panthenol

INACTIVE INGREDIENT

Water
Alcohol
Glycerin
PEG-60 Hydrogenated Castor Oil
Tromethamine
Carbomer
Trideceth-10
Fragrance
Butylene Glycol
1,2-Hexanediol
Caprylyl Glycol
Brassica Oleracea Italica (Broccoli) Extract
Illicium Verum (Anise) Fruit Extract
Sodium Hyaluronate
Geraniol
Linalool
Citronellol
Hexyl Cinnamal
Limonene

PURPOSE

Helps relieve and revitalizing scalp.

keep out of reach of the children

INDICATIONS AND USAGE

After shampooing and before drying, apply an appropriate am
ount to the scalp in a wet state using your fingers and massage
so that it is fully absorbed. It ries commended to use it at least 3
times a week.

WARNINGS

1. If you have any of the following side effetsc while using, you
should stop using, iatnd if you continue to use, iytour sympt
oms will worsen, so consult your dermatologist.
-If there are side effects such as red spots, swelling, itching, irrita
tion during use.
-If the application area has the above side efftesc
due to direct sunlight
2. Do not use on areas with wounds, eczema or dermatitis.
3. Precautions for stoarge and handling
- Be sure to close the cap taefr use.
- Do not store where children may reach.
- Store in a place with high or low tempaeturre and out of dire
ct sunlight.
4. In case of contact with eyes, rinse immediately and consult
a physician.
5. People who have ever had allergies, please consult your dotc
or or pharmacist before use
6. Do not use on children under 3 years ogfe a.
7. People with hypersensitivity to salicylic acid or who hasa bdei
tes, blood circulation disorders, renala filure, infection, redness,
those who are pregnant or may become pregnant should av
oid using the pdrouct as the current symptoms may worsen
a fter use, such as skin or body hypersensitivity or skin adverse
reatcions (edema, inflammation, etc.). So please avoid using it.
- Product Liability Act (PL Act): Before use, be sure to read the
instructions for use and precautions.

DOSAGE AND ADMINISTRATION

for external use only